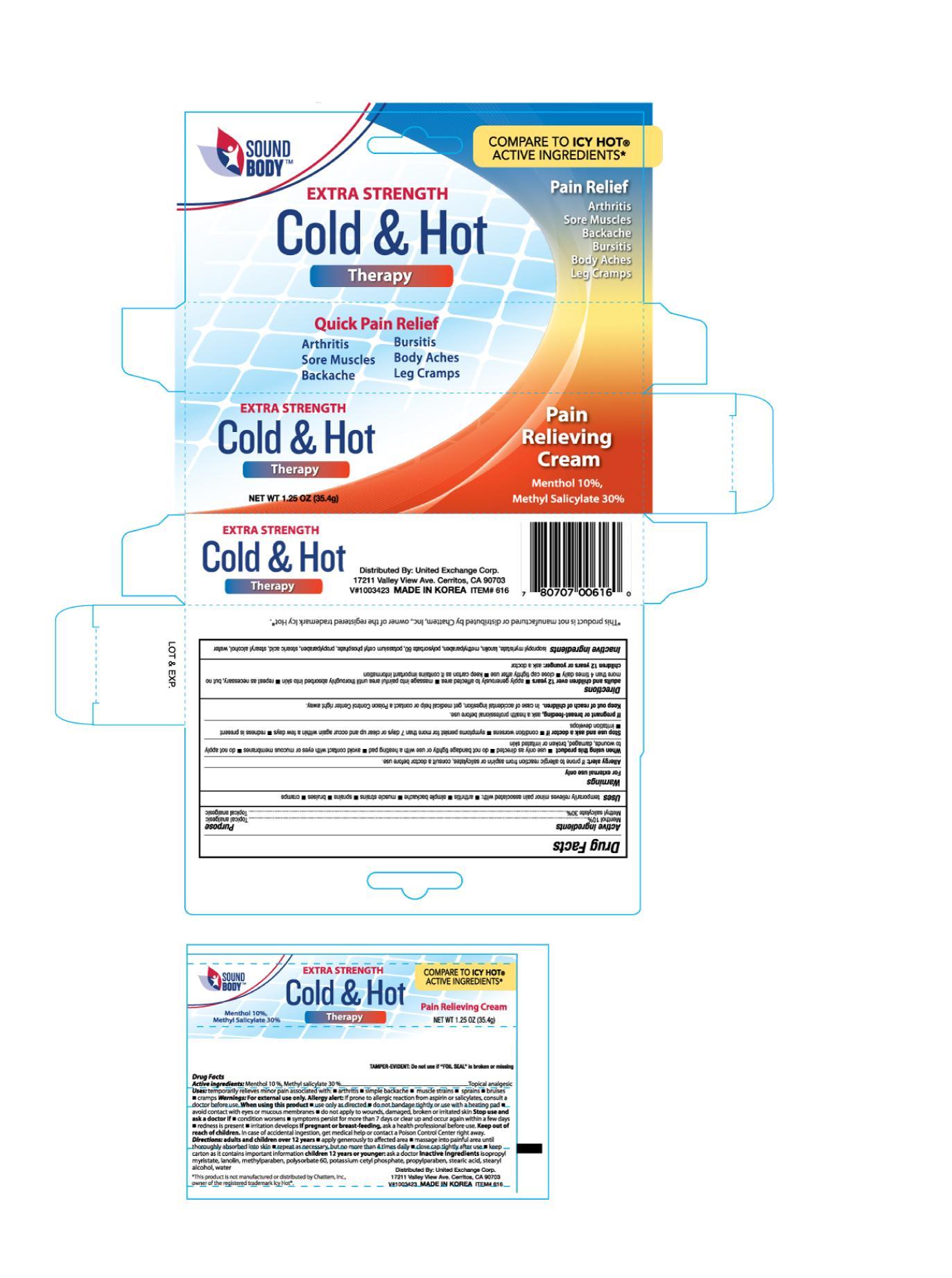 DRUG LABEL: Sound Body Extra Strength Cold and Hot
NDC: 65923-616 | Form: CREAM
Manufacturer: United Exchange Corp.
Category: otc | Type: HUMAN OTC DRUG LABEL
Date: 20150224

ACTIVE INGREDIENTS: MENTHOL 10 g/100 g; METHYL SALICYLATE 30 g/100 g
INACTIVE INGREDIENTS: ISOPROPYL MYRISTATE; LANOLIN; METHYLPARABEN; POLYSORBATE 60; POTASSIUM CETYL PHOSPHATE; PROPYLPARABEN; STEARIC ACID; STEARYL ALCOHOL; WATER

Active ingredients Purpose

Menthol 10%................................................................................ Topical analgesic

Methyl salcylate 30%..................................................................... Topical analgesic

Uses

temporarily relieves minor pain associated with:

- arthritis
- simple backache
- muscle strains
- sprains
- bruises
- cramps

Warnings

For external use only

Allergy alert: if prone to allergic reaction from aspirin or salcylates, consult a doctor before use

When using this product

- use only as directed
- do not bandage tightly or use with a heating pad
- avoid contact with eyes or mucous membranes
- do not apply to wounds, damaged, broken or irritated skin

Stop use and ask a doctor if

- condition worsens
- symptoms persist for more than 7 days or clear up and occur again wtihin a few days
- redness is present
- irritation develops

Stop use and ask a doctor if

- condition worsens
- symptoms perist for more than 7 days or clear up and occur again within a few days
- redness is present
- irritation develops

PREGNANCY OR BREAST FEEDING

If pregnant or breast-feeding, ask a health progessional before use.

Keep out of reach of children. In case of accidental ingestion, get medical help or contact a Poison Control Center right away.

Directions

adults and children over 12 years

- apply generously to affected area
- massage into painful area until thoroughly absorbed into skin
- repeat as necessary, but no more than 4 times daily
- close cap tightly after use
- keep carton as it contains important information

children 12 years or younger: ask a doctor

Inactive ingredients

isopropyl myristate, lanolin, methylparaben, polysorbate 60, potassium cetyl phosphate, propylparaben, stearic acid, stearyl alcohol, water

DOSAGE AND ADMINISTRATION

DISTRIBUTED BY:

UNITED EXCHANGE CORP.

17211 VALLEY VIEW AVE.

CERRITOS, CA 90703

MADE IN KOREA